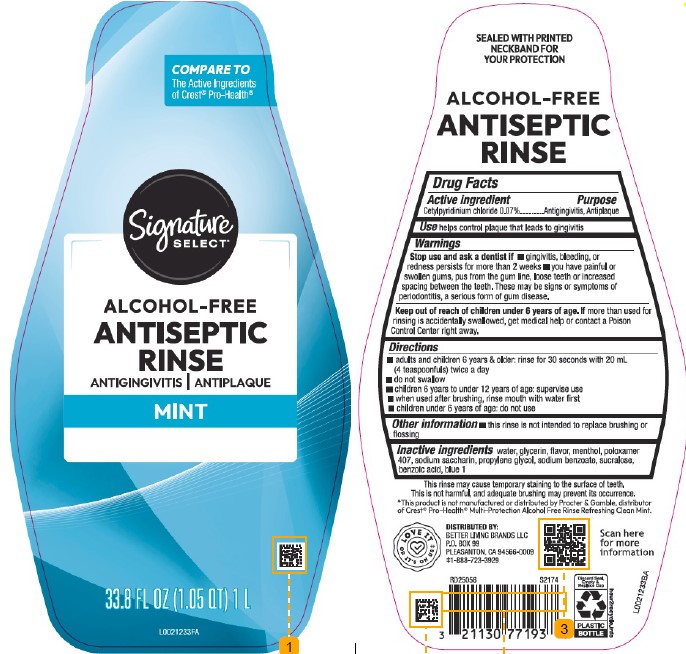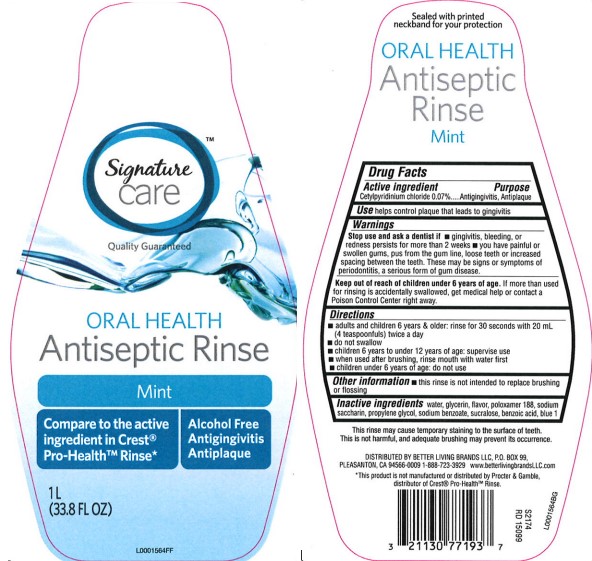 DRUG LABEL: Mint
NDC: 21130-299 | Form: MOUTHWASH
Manufacturer: Better Living Brands, LLC
Category: otc | Type: HUMAN OTC DRUG LABEL
Date: 20260223

ACTIVE INGREDIENTS: CETYLPYRIDINIUM CHLORIDE 0.7 mg/1 mL
INACTIVE INGREDIENTS: WATER; GLYCERIN; MENTHOL, UNSPECIFIED FORM; POLOXAMER 407; SACCHARIN SODIUM; PROPYLENE GLYCOL; SODIUM BENZOATE; SUCRALOSE; BENZOIC ACID; FD&C BLUE NO. 1

Signature Care_Signature Select 299.006/299AM
Multi Action Alcohol Free Antiseptic Rinse w/CPC

Tamper Evident Statement

SEALED WITH PRINTED NECKBAND FOR YOUR PROTECTION

Claim

ALCOHOL-FREE

ANTISEPTIC RINSE

Active Ingredient

Cetylpyridinium chloride 0.07%

Purpose

Antigingivitis, Antiplaque

Use

helps control plaque that leads to gingivitis

Warnings

for this product

Stop use and ask a dentist if

- gingivitis, bleeding, or redness persists for more than 2 weeks
- you have painful or swollen gums, pus from the gum line, loose teeth or increased spacing between the teeth. These may be signs or symptoms of periodontitis, a serious form of gum disease

Keep out of reach of children under 6 years of age.

If more than used for rinsing is accidentally swallowed, get medical help or contact a Poison Control Center right away.

Directions

- adults and children 6 years & older: rinse for 30 seconds with 20 mL (4 teaspoonfuls) twice a day
- do not swallow
- children 6 years to under 12 years of age: supervise use
- when used after brushing, rinse mouth with water first
- children under 6 years of age: do not use

Other information

- this rinse is not intended to replace brushing or flossing

Inactive ingredients

water, glycerin, flavor, menthol, poloxamer 407, sodium saccharin, propylene glycol, sodium benzoate, sucralose, benzoic acid, blue 1

Disclaimer

This rinse may cause temporary staining to the surface of teeth.

This is not harmful, and adequate brushing may prevent its occurrence.

*This product is not manufactured or distributed by Procter & Gamble, distributor of Crest®Pro-Health®Multi-Protection Alcohol Free Rinse Refreshing Clean Mint.

DISTRIBUTED BY:

BETTER LIVING BRANDS LLC,

P.O. BOX 99

PLEASANTON, CA 94566-0009

1-888-723-3929

LOVE IT OR IT'S ON US

Scan here for more information

Discard Seal, Empty & Replace Cap

PLASTIC BOTTLE

how2recycle.info

principal display panel

Signature CARE™

Quality Guaranteed

ORAL HEALTH

Antiseptic Rinse

Mint

Alcohol Free

Antigingivitis Antiplaque

Compare to active ingredient in Crest Pro-Health Rinse*

1L (33.8 FL OZ)

PRINCIPAL DISPLAY PANEL

COMPARE TO

The Active Ingredients of Crest®Pro-Health®

Signature

SELECT®

ALCOHOL-FREE

ANTISEPTIC

RINSE

ANTIGINGIVITS/ANTIPLAQUE

MINT

33.8 FL OZ (1.05 QT) 1 L